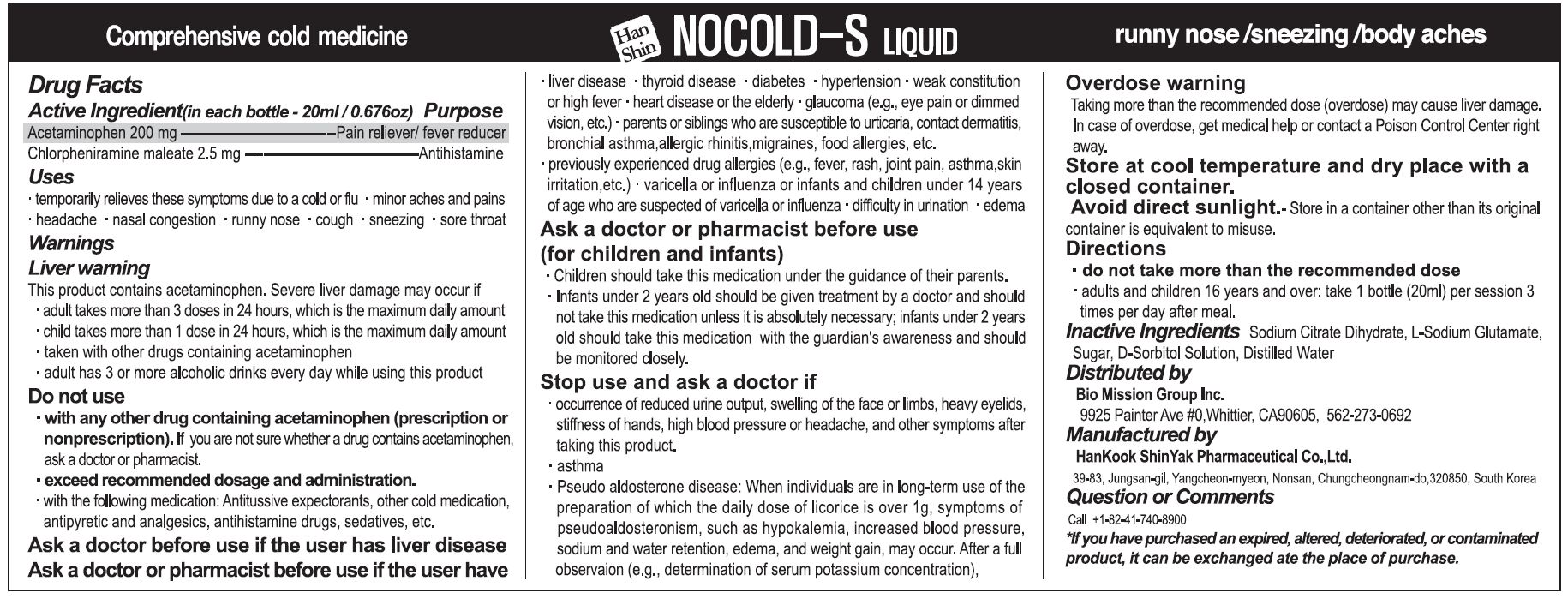 DRUG LABEL: NOCOLD-S
NDC: 72988-0033 | Form: LIQUID
Manufacturer: Lydia Co., Ltd.
Category: otc | Type: HUMAN OTC DRUG LABEL
Date: 20230705

ACTIVE INGREDIENTS: CHLORPHENIRAMINE MALEATE 2.5 mg/20 mL; ACETAMINOPHEN 200 mg/20 mL
INACTIVE INGREDIENTS: TRISODIUM CITRATE DIHYDRATE

ACTIVE INGREDIENT

Acetaminophen, Chlorpheniramine Maleate

PURPOSE

temporarily relieves thee symptoms due to cold or flu

minor aches and pains headache, nasal congestion, runny nose, cough, sneezing, sore throat

Keep out of reach of children

INDICATIONS AND USAGE

■ Adult and children 16 years and over: take 1 bottle (20ml) per session 3 times per day after meal

WARNINGS

see product label

INACTIVE INGREDIENT

sodium citrate dihydrate, L-sodium glutamate, sugar, d-sorbitol solution, distilled water

DOSAGE AND ADMINISTRATION

for oral use